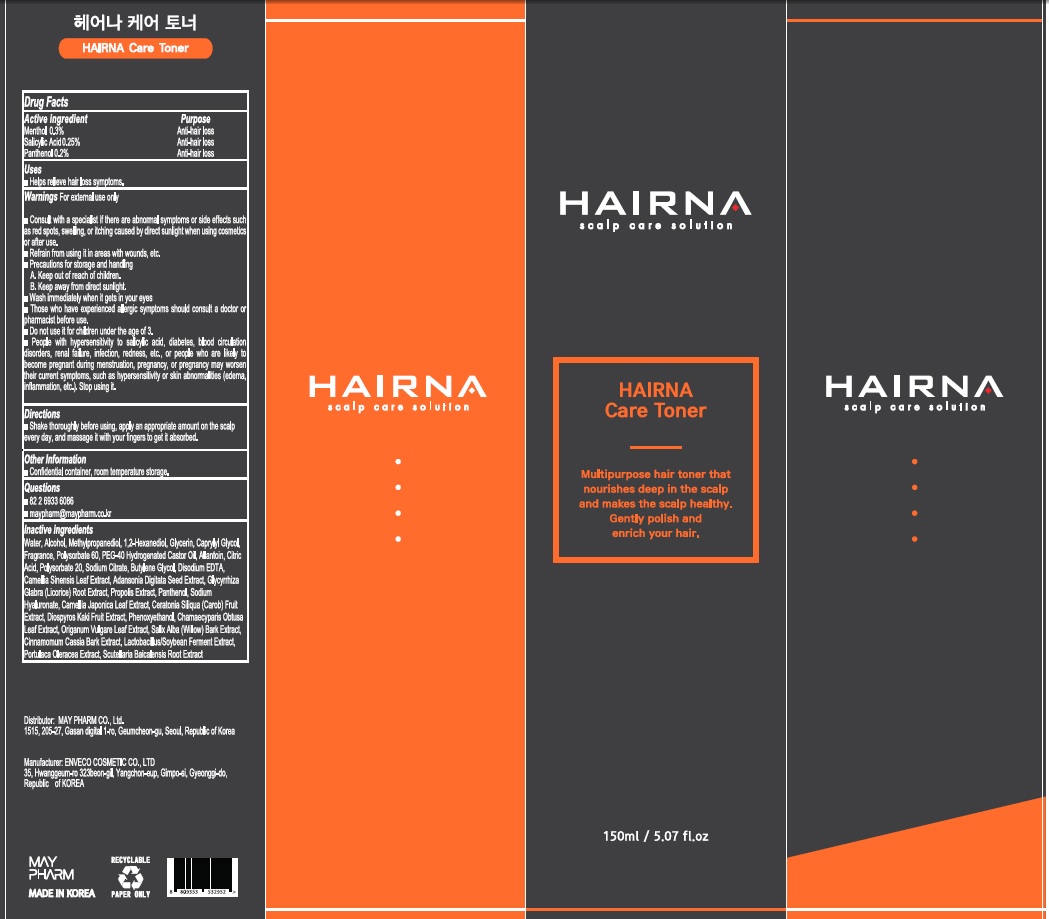 DRUG LABEL: HAIRNA Care Toner
NDC: 82344-050 | Form: LIQUID
Manufacturer: MAYPHARM
Category: otc | Type: HUMAN OTC DRUG LABEL
Date: 20211129

ACTIVE INGREDIENTS: Menthol 0.3 g/100 mL; Salicylic Acid 0.25 g/100 mL; Panthenol 0.20 g/100 mL
INACTIVE INGREDIENTS: Water; Alcohol

ACTIVE INGREDIENTS

Menthol 0.3%
Salicylic Acid 0.25%
Panthenol 0.20%

PURPOSE

Anti-hair loss

Uses

■ Helps relieve hair loss symptoms.

WARNINGS

For external use only

■ Consult with a specialist if there are abnormal symptoms or side effects such as red spots, swelling, or itching caused by direct sunlight when using cosmetics or after use.
■ Refrain from using it in areas with wounds, etc.
■ Precautions for storage and handling
A. Keep out of reach of children.
B. Keep away from direct sunlight.
■ Wash immediately when it gets in your eyes
■ Those who have experienced allergic symptoms should consult a doctor or pharmacist before use.
■ Do not use it for children under the age of 3.
■ People with hypersensitivity to salicylic acid, diabetes, blood circulation disorders, renal failure, infection, redness, etc., or people who are likely to become pregnant during menstruation, pregnancy, or pregnancy may worsen their current symptoms, such as hypersensitivity or skin abnormalities (edema, inflammation, etc.). Stop using it.

KEEP OUT OF REACH OF CHILDREN

Directions

■ Shake thoroughly before using, apply an appropriate amount on the scalp every day, and massage it with your fingers to get it absorbed.

Other Information

■ Confidential container, room temperature storage.

Questions

■ 82 2 6933 6086
■ maypharm@maypharm.co.kr

INACTIVE INGREDIENTS

Water, Alcohol, Methylpropanediol, 1,2-Hexanediol, Glycerin, Caprylyl Glycol, Fragrance, Polysorbate 60, PEG-40 Hydrogenated Castor Oil, Allantoin, Citric Acid, Polysorbate 20, Sodium Citrate, Butylene Glycol, Disodium EDTA, Camellia Sinensis Leaf Extract, Adansonia Digitata Seed Extract, Glycyrrhiza Glabra (Licorice) Root Extract, Propolis Extract, Panthenol, Sodium Hyaluronate, Camellia Japonica Leaf Extract, Ceratonia Siliqua (Carob) Fruit Extract, Diospyros Kaki Fruit Extract, Phenoxyethanol, Chamaecyparis Obtusa Leaf Extract, Origanum Vulgare Leaf Extract, Salix Alba (Willow) Bark Extract, Cinnamomum Cassia Bark Extract, Lactobacillus/Soybean Ferment Extract, Portulaca Oleracea Extract, Scutellaria Baicalensis Root Extract